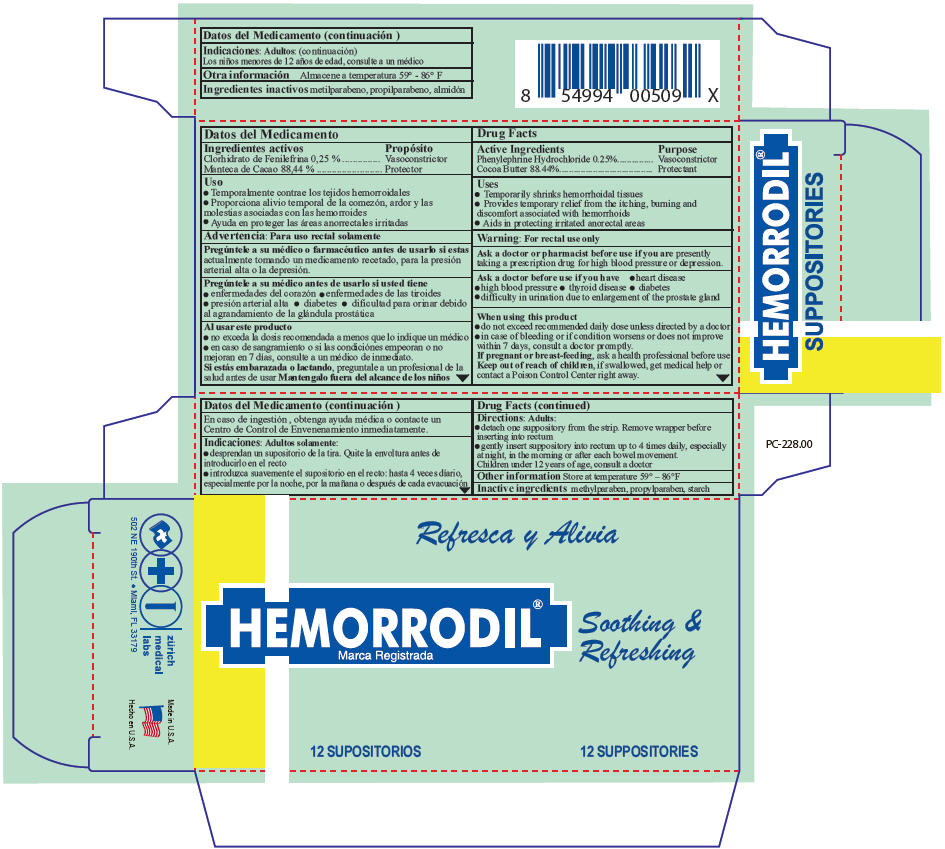 DRUG LABEL: Hemorrodil
NDC: 61357-135 | Form: SUPPOSITORY
Manufacturer: ZURICH MEDICAL LABS, LLC
Category: otc | Type: HUMAN OTC DRUG LABEL
Date: 20140311

ACTIVE INGREDIENTS: PHENYLEPHRINE HYDROCHLORIDE 5 mg/1 1; COCOA BUTTER 1768.8 mg/1 1
INACTIVE INGREDIENTS: STARCH, CORN; METHYLPARABEN; PROPYLPARABEN

Hemorrodil® Supositorios

Drug Facts

ACTIVE INGREDIENT

Active Ingredients | Purpose
Phenylephrine Hydrochloride 0.25% | Vasoconstrictor
Cocoa Butter 88.44% | Protectant

Uses

- Temporarily shrinks hemorrhoidal tissues
- Provides temporary relief from the itching, burning and discomfort associated with hemorrhoids
- Aids in protecting irritated anorectal areas

Warning

For rectal use only

Ask a doctor or pharmacist before use if you are presently taking a prescription drug for high blood pressure or depression.

Ask a doctor before use if you have

- heart disease
- high blood pressure
- thyroid disease
- diabetes
- difficulty in urination due to enlargement of the prostate gland

When using this product

- do not exceed recommended daily dose unless directed by a doctor
- in case of bleeding or if condition worsens or does not improve within 7 days, consult a doctor promptly.

PREGNANCY OR BREAST FEEDING

If pregnant or breast-feeding, ask a health professional before use

Keep out of reach of children, if swallowed, get medical help or contact a Poison Control Center right away.

Directions

Adults

- detach one suppository from the strip. Remove wrapper before inserting into rectum
- gently insert suppository into rectum up to 4 times daily, especially at night, in the morning or after each bowel movement.

Children under 12 years of age, consult a doctor

Other information

Store at temperature 59° – 86°F

Inactive ingredients

methylparaben, propylparaben, starch

PRINCIPAL DISPLAY PANEL - 12 Suppository Blister Pack Carton

HEMORRODIL®

Soothing &
Refreshing

12 SUPPOSITORIES